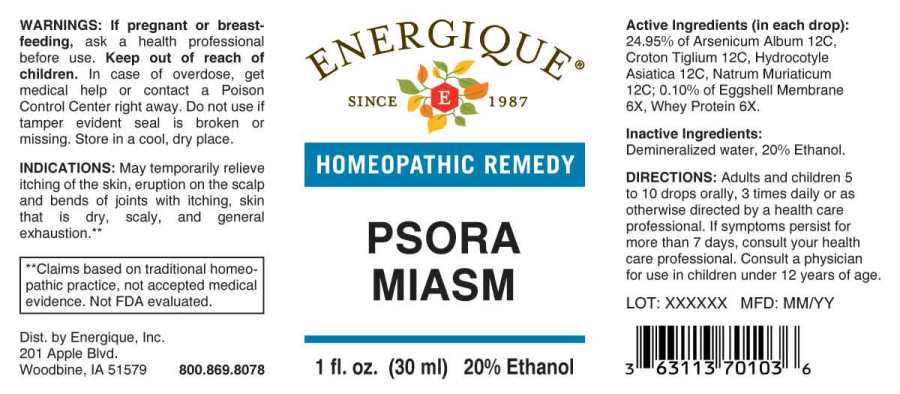 DRUG LABEL: Psora Miasm
NDC: 44911-0270 | Form: LIQUID
Manufacturer: Energique, Inc.
Category: homeopathic | Type: HUMAN OTC DRUG LABEL
Date: 20230316

ACTIVE INGREDIENTS: EGG SHELL MEMBRANE 6 [hp_X]/1 mL; WHEY 6 [hp_X]/1 mL; ARSENIC TRIOXIDE 12 [hp_C]/1 mL; CROTON TIGLIUM SEED 12 [hp_C]/1 mL; CENTELLA ASIATICA 12 [hp_C]/1 mL; SODIUM CHLORIDE 12 [hp_C]/1 mL
INACTIVE INGREDIENTS: WATER; ALCOHOL

Drug Facts:

ACTIVE INGREDIENTS:

(in each drop): 24.95% of Arsenicum Album 12C, Croton Tiglium 12C, Hydrocotyle Asiatica 12C, Natrum Muriaticum 12C; 0.10% of Eggshell Membrane 6X, Whey Protein 6X.

INDICATIONS:

May temporarily relieve itching of the itching skin, eruption on the scalp and bends of joints with itching, skin that is dry, scaly, and general exhaustion.**

**Claims based on traditional homeopathic practice, not accepted medical evidence. Not FDA evaluated.

WARNINGS:

If pregnant or breast-feeding, ask a health professional before use.

Keep out of reach of children. In case of overdose, get medical help or contact a Poison Control Center right away.

Do not use if tamper evident seal is broken or missing. Store in a cool, dry place.

Keep out of reach of children. In case of overdose, get medical help or contact a Poison Control Center right away.

DIRECTIONS:

Adults and children 5 to 10 drops orally, 3 times daily or as otherwise directed by a health care professional. If symptoms persist for more than 7 days, consult your health care professional. Consult a physician for use in children under 12 years of age.

INDICATIONS:

May temporarily relieve itching of the itching skin, eruption on the scalp and bends of joints with itching, skin that is dry, scaly, and general exhaustion.**

**Claims based on traditional homeopathic practice, not accepted medical evidence. Not FDA evaluated.

INACTIVE INGREDIENTS:

Demineralized water, 20% Ethanol.

QUESTIONS:

Dist. by Energique, Inc.

201 Apple Blvd.

Woodbine, IA 51579 800.869.8078

PACKAGE LABEL DISPLAY:

ENERGIQUE

SINCE 1987

HOMEOPATHIC REMEDY

PSORA

MIASM

1 fl. oz. (30 ml)